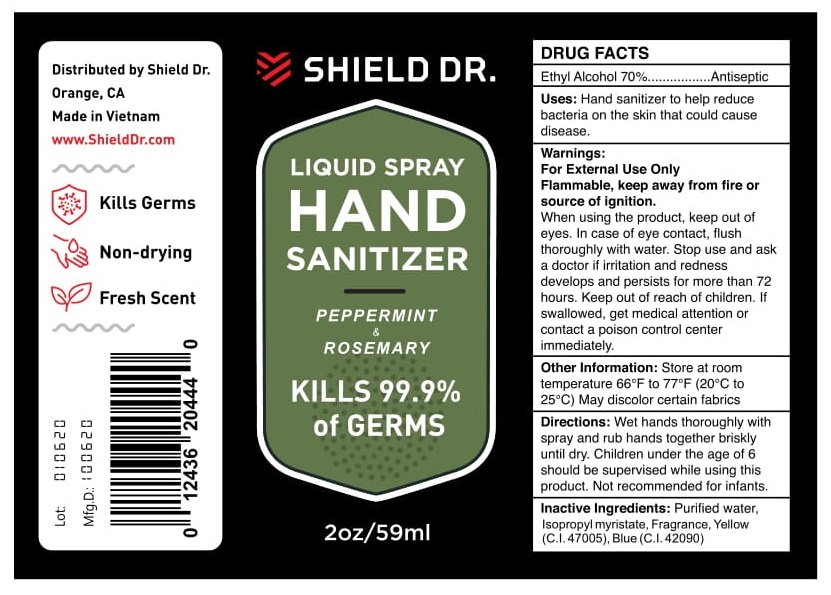 DRUG LABEL: Shield Dr.
NDC: 79633-304 | Form: LIQUID
Manufacturer: MEDIPHARCO PHARMACEUTICAL JOINT STOCK COMPANY
Category: otc | Type: HUMAN OTC DRUG LABEL
Date: 20200819

ACTIVE INGREDIENTS: ALCOHOL 70 mL/100 mL
INACTIVE INGREDIENTS: WATER; ISOPROPYL MYRISTATE; ROSEMARY OIL; POLYOXYL 40 HYDROGENATED CASTOR OIL; PEPPERMINT OIL; FD&C BLUE NO. 1; CARMOISINE; D&C YELLOW NO. 10

PURPOSE

Antiseptic

INACTIVE INGREDIENT

Purified water, Isopropyl myristate, Fragrance, Yellow (C.I. 47005), Blue (C.I.42090)

INDICATIONS AND USAGE

Hand sanitizer to help reduce bacteria on the skin it could cause disease

DOSAGE AND ADMINISTRATION

Wet hand thoroughly with spray and rub hand together briskly until dry. Children under the age of 6 should be supervised while using this product. Not recommended for infants.

WARNINGS

For external use only.

Flammable, keep away from fire or source of ignition.

KEEP OUT OF REACH OF CHILDREN

If swallowed, get medical attention or contact poison control center immediately

STORAGE AND HANDLING

Store at room temperature 66o F to 77oF (20oC to 25oC)

PACKAGE LABEL

59ml NDC: 79633-304-59